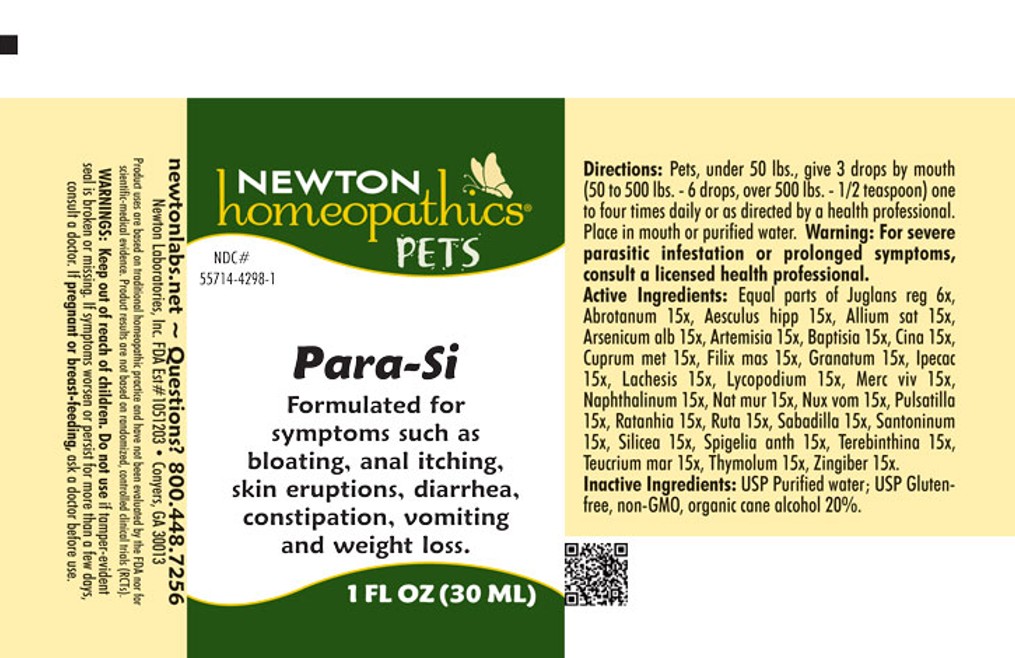 DRUG LABEL: Para-Si
NDC: 55714-4298 | Form: LIQUID
Manufacturer: Newton Laboratories, Inc.
Category: homeopathic | Type: OTC ANIMAL DRUG LABEL
Date: 20250908

ACTIVE INGREDIENTS: Artemisia Abrotanum Flowering Top 15 [hp_X]/1 mL; Horse Chestnut 15 [hp_X]/1 mL; Garlic 15 [hp_X]/1 mL; Arsenic Trioxide 15 [hp_X]/1 mL; Artemisia Vulgaris Root 15 [hp_X]/1 mL; Baptisia Tinctoria Root 15 [hp_X]/1 mL; Artemisia Cina Flower 15 [hp_X]/1 mL; Copper 15 [hp_X]/1 mL; Dryopteris Filix-mas Root 15 [hp_X]/1 mL; Punica Granatum Root Bark 15 [hp_X]/1 mL; Ipecac 15 [hp_X]/1 mL; Lachesis Muta Venom 15 [hp_X]/1 mL; Lycopodium Clavatum Spore 15 [hp_X]/1 mL; Mercury 15 [hp_X]/1 mL; Naphthalene 15 [hp_X]/1 mL; Sodium Chloride 15 [hp_X]/1 mL; Strychnos Nux-vomica Seed 15 [hp_X]/1 mL; Pulsatilla Vulgaris 15 [hp_X]/1 mL; Krameria Lappacea Root 15 [hp_X]/1 mL; Ruta Graveolens Flowering Top 15 [hp_X]/1 mL; Schoenocaulon Officinale Seed 15 [hp_X]/1 mL; Santonin 15 [hp_X]/1 mL; Silicon Dioxide 15 [hp_X]/1 mL; Spigelia Anthelmia 15 [hp_X]/1 mL; Turpentine Oil 15 [hp_X]/1 mL; Teucrium Marum 15 [hp_X]/1 mL; Thymol 15 [hp_X]/1 mL; Ginger 15 [hp_X]/1 mL; Juglans Regia Leaf 3 [hp_X]/1 mL
INACTIVE INGREDIENTS: Alcohol

Parasites

PRODUCT NAME & INDICATIONS SECTION

Formulated for symptoms such as bloating, anal itching, skin eruptions, diarrhea, constipation, vomiting and weight loss.

DIRECTION SECTION

Pets, under 50 lbs., give 3 drops by mouth (50 to 500 lbs. - 6 drops, over 500 lbs. - 1/2 teaspoon) one to four times daily or as directed by a health professional. Place in mouth or purified water. Warning: For severe parasitic infestation or prolonged symptoms, consult a licensed health professional.

ACTIVE INGREDIENT SECTION

Equal parts of Juglans reg 6x, Abrotanum 15x, Aesculus hipp 15x, Allium sat 15x, Arsenicum alb 15x, Artemisia 15x, Baptisia 15x, Cina 15x, Cuprum met15x, Filix mas 15x, Granatum 15x, Ipecac 15x, Lachesis 15x, Lycopodium 15x, Merc viv 15x, Naphthalinum 15x, Nat mur 15x, Nux vom15x, Pulsatilla 15x, Ratanhia 15x, Ruta 15x, Sabadilla 15x, Santoninum 15x, Silicea 15x, Spigelia anth 15x, Terebinthina 15x,Teucrium mar 15x, Thymolum 15x, Zingiber 15x.

INACTIVE INGREDIENTS SECTION

USP Purified Water; USP Gluten-free, non-GMO, organic cane alcohol 20%.

QUESTIONS SECTION

newtonlabs.net - Questions? 800.448.7256 Newton Laboratories, Inc. FDA Est # 1051203 - Conyers, GA 30013

WARNINGS SECTION

WARNINGS: Keep out of reach of children. Do not use if tamper-evident seal is broken or missing. If symptoms worsen or persist for more than a few days, consult a doctor. If pregnant or breast-feeding, as a doctor before use.

PREGNANCY OR BREAST FEEDING SECTION

If pregnant or breast-feeding, ask a doctor before use.

KEEP OUT OF REACH OF CHILDREN SECTION

Keep out of reach of children.